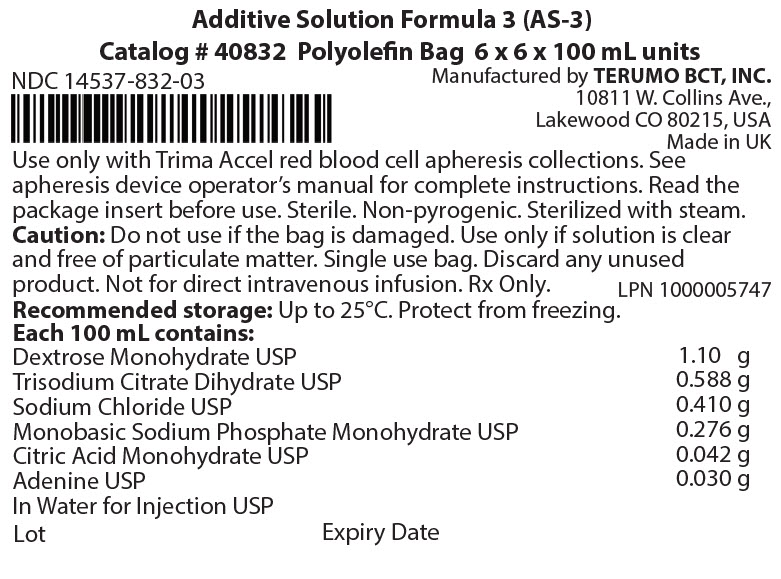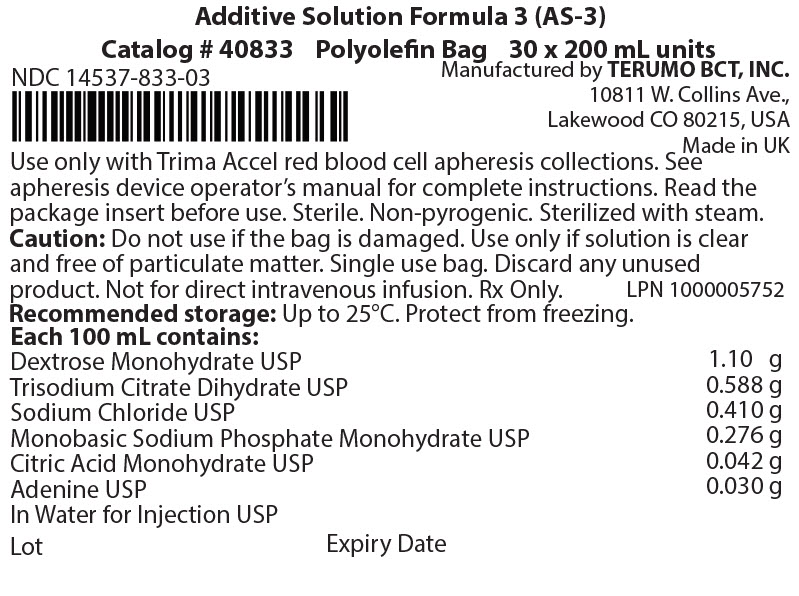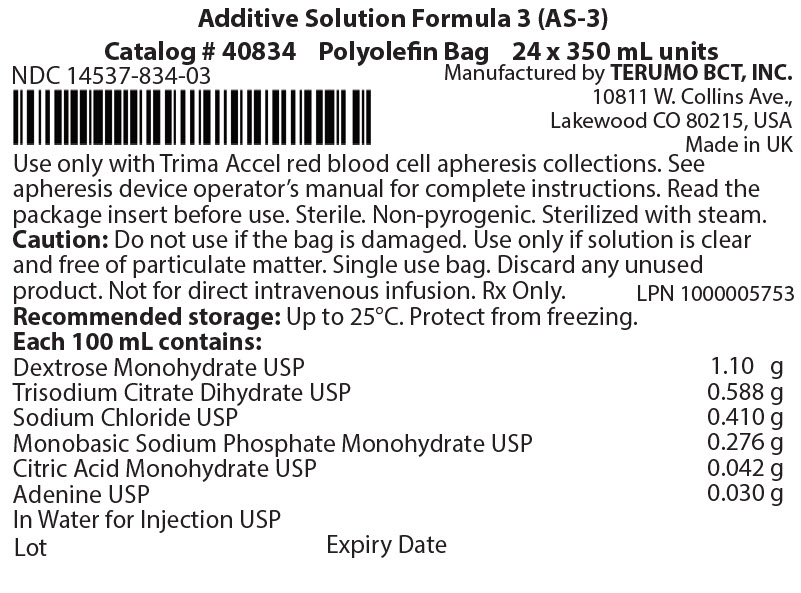 DRUG LABEL: Additive Formula 3
NDC: 14537-832 | Form: SOLUTION
Manufacturer: Terumo BCT, Ltd
Category: prescription | Type: HUMAN PRESCRIPTION DRUG LABEL
Date: 20260130

ACTIVE INGREDIENTS: Dextrose Monohydrate 1.1 g/100 mL; TRISODIUM CITRATE DIHYDRATE 0.59 g/100 mL; Sodium Chloride 0.41 g/100 mL; SODIUM PHOSPHATE, MONOBASIC, MONOHYDRATE 0.28 g/100 mL; Citric Acid Monohydrate 0.042 g/100 mL; Adenine 0.03 g/100 mL
INACTIVE INGREDIENTS: Water

HIGHLIGHTS OF PRESCRIBING INFORMATION

These highlights do not include all the information needed to use ADDITIVE SOLUTION FORMULA 3 (AS-3) safely and effectively. See full prescribing information for ADDITIVE SOLUTION FORMULA 3 (AS-3).
ADDITIVE SOLUTION FORMULA 3 (AS-3)
Sterile Fluid
Polyolefin Bag
Initial U.S. Approval: 2002

1 INDICATIONS AND USAGE

Use only with Trima Accel red blood cell (RBC) apheresis collections. (1)

2 DOSAGE AND ADMINISTRATION

- AS-3 is added to tubing sets after apheresis collections, after the donor has been disconnected. (2)
- AS-3 may only be used with the Trima Accel apheresis device. For instructions on the use of the solution see the device operator's manual. (2.1)
- Follow the directions for connecting the AS-3 bag to the tubing set of a blood collection system. (2.2)

3 DOSAGE FORMS AND STRENGTHS

- 100 mL, 200 mL, or 350 mL sterile fluid in a Polyolefin bag. (3)

4 CONTRAINDICATIONS

- DO NOT INFUSE AS-3 DIRECTLY TO THE DONOR. (4)

5 WARNINGS AND PRECAUTIONS

- Verify that the AS-3 bag has been securely attached to the system tubing set. Use aseptic technique throughout all procedures to ensure product quality. (5)
- Do not reuse. Discard unused or partially used solution bags.

6 ADVERSE REACTIONS

Citrate reactions or toxicity may occur with the infusion of blood containing citrate. The recipient of the blood containing citrate should be monitored for the signs and symptoms of citrate toxicity. (6)

To report SUSPECTED ADVERSE REACTIONS, contact Terumo BCT, Inc. at 1-877-339-4228 or FDA at 1-800-FDA-1088 or www.fda.gov/medwatch.

FULL PRESCRIBING INFORMATION

1 INDICATIONS AND USAGE

Use only with Trima Accel red blood cell (RBC) apheresis collections. [See Dosage and Administration (2).]

2 DOSAGE AND ADMINISTRATION

2.1 General Dosing Information

ADDITIVE SOLUTION FORMULA 3 (AS-3) is connected to the tubing set used for an apheresis RBC collection procedure after the collection has been completed.

- For automated RBC procedures, the recommended dose is determined by the apheresis device and metered into the tubing set by the apheresis device.
- To add the product manually, refer to the apheresis system operator's manual to determine the recommended dose.

For instructions on the use of the solution with the apheresis device and tubing set, see the device operator's manual.

2.2 Administration

Directions for connecting the ADDITIVE SOLUTION FORMULA 3 (AS-3) bag to the apheresis device.

Automated RBC additive solution procedures:

Connect ADDITIVE SOLUTION FORMULA 3 (AS-3) after the collection is over and the donor is disconnected. For automated addition of the product, the system will prompt you to connect the bag.

1. Remove the overwrap by pulling down at notch, and remove the AS-3 bag.
2. Before use, perform the following checks:
  - Ensure that the solution is the ADDITIVE SOLUTION FORMULA 3 (AS-3) and is within the expiration date.
  - Inspect the bag in good light. Do not use if the container is damaged, leaking or if there is any visible sign of deterioration. Check for leaks by gently squeezing the bag. If leaks are found, discard the bag.
  - Inspect the solution in good light. Use only if solution is clear and free of particulate matter. Bags showing cloudiness, haze, or particulate matter should not be used.
  - Protect from sharp objects.
3. Remove the protective cap from the port on the bag.
4. Connect the bag to the complementary luer of the apheresis device tubing set using aseptic technique and hang the solution.
5. Break the frangible connector. When you break frangible connectors, bend them in both directions to ensure that you break them completely. Failure to do so may result in restricted flow.
6. Proceed according to the apheresis device operator's manual.

Manual RBC additive solution procedures:

Connect ADDITIVE SOLUTION FORMULA 3 (AS-3) after the collection is over and the donor is disconnected.

1. Seal the RBC product lines as close to the cassette as possible.
2. Remove the overwrap by pulling down at notch, and remove the ADDITIVE SOLUTION FORMULA 3 bag.
3. Before use, perform the following checks:
  - Ensure that the solution is the ADDITIVE SOLUTION FORMULA 3 (AS-3) and is within the expiration date.
  - Inspect the bag in good light. Do not use if the container is damaged, leaking or if there is any visible sign of deterioration. Check for leaks by gently squeezing the bag. If leaks are found, discard the bag.
  - Inspect the solution in good light. Use only if solution is clear and free of particulate matter. Bags showing cloudiness, haze, or particulate matter should not be used.
  - Protect from sharp objects.
4. Remove the protective cap from the port on the bag.
5. Insert the spike of the apheresis device tubing set into the spike port of the solution bag using aseptic technique and then hang the solution.
6. Proceed according to the apheresis device operator's manual.

3 DOSAGE FORMS AND STRENGTHS

100 mL, 200 mL and 350 mL ADDITIVE SOLUTION FORMULA 3 (AS-3) products are sterile solutions in a Polyolefin bag. Each 100 mL contains: Dextrose Monohydrate USP 1.10 g; Trisodium Citrate Dihydrate USP 0.59 g; Sodium Chloride USP 0.41 g; Monobasic Sodium Phosphate Monohydrate USP 0.28 g; Citric Acid Monohydrate USP 0.042 g; Adenine USP 0.03 g; and Water for Injection USP.

4 CONTRAINDICATIONS

DO NOT INFUSE ADDITIVE SOLUTION FORMULA 3 (AS-3) DIRECTLY TO THE DONOR.

5 WARNINGS AND PRECAUTIONS

- Verify that the AS-3 bag has been securely attached to the system tubing set. Use aseptic technique throughout all procedures to ensure product quality.
- Do not reuse. Discard unused or partially used solution bags.

6 ADVERSE REACTIONS

Citrate reactions or toxicity may occur with the infusion of blood products to patients. The recipient of the blood containing citrate should be monitored for the signs and symptoms of citrate toxicity. The signs and symptoms of citrate toxicity begin with paresthesia, a "tingling" sensation around the mouth or in the extremities, followed by severe reactions that are characterized by hypotension and possible cardiac arrhythmia. Citrate toxicity may occur more frequently in patients who are hypothermic, have impaired liver or renal function, or have low calcium levels because of an underlying disease.

8 USE IN SPECIFIC POPULATIONS

ADDITIVE SOLUTION FORMULA 3 (AS-3) has not been studied in controlled clinical trials with specific populations.

11 DESCRIPTION

ADDITIVE SOLUTION FORMULA 3 (AS-3) is designed to be added to packed RBC collected in apheresis procedures, and acts to preserve and extend the shelf life of packed RBC products for later transfusion to patients. The solution is intended to be metered by an apheresis device during apheresis procedures or added manually after a collection.

Additive Solution Formula 3 (AS-3) is a clear solution that is steam-sterilized and non-pyrogenic. It does not contain bacteriostatic or antimicrobial agents.

The formulas of the active ingredients are provided in Table 1.

Table 1: Active Ingredients
Ingredients | Molecular Formula | Molecular Weight
Dextrose Monohydrate USP | C6H12O6 ∙ H2O | 198.17
Trisodium Citrate Dihydrate USP | C6H9Na3O9 | 294.10
Sodium Chloride USP | NaCl | 58.44
Monobasic Sodium Phosphate Monohydrate USP | NaH2PO4 ∙ H2O | 137.99
Citric Acid Monohydrate USP | C6H807 ∙ H2O | 210.14
Adenine USP | C5H5N5 | 135.13
Water for Injection USP | H2O | 18.00

Each 100 mL of ADDITIVE SOLUTION FORMULA 3 (AS-3) contains: Dextrose Monohydrate USP 1.10 g; Trisodium Citrate Dihydrate USP 0.59 g; Sodium Chloride USP 0.41 g; Monobasic Sodium Phosphate Monohydrate USP 0.28 g; Citric Acid Monohydrate USP 0.042 g; Adenine USP 0.03 g; and Water for Injection USP.

ADDITIVE SOLUTION FORMULA 3 is available in three volumes: 100 mL, 200 mL and 350 mL.

The 100 mL bags are individually wrapped with a clear plastic film. Six individually wrapped bags are then vacuum-sealed in a foil pouch, which serves as a vapor barrier to prevent water loss during storage. After you remove the individual solution bags from the foil pouch, you can either leave them in the clear plastic film or remove and discard it. Once the foil pouch has been opened, use all six of the solution bags within 2 weeks.

The 200 mL and 350 mL bags are individually wrapped with a clear plastic film. These larger volumes do not require the additional vapor barrier. Once the clear plastic film has been removed, use the solution within 2 weeks.

The Polyolefin bag is not made with natural rubber latex.

The bag is made from a multilayered film. It contains materials that have been tested to demonstrate the suitability of the container for storing pharmaceutical solutions. The bag is nontoxic and biologically inert. The bag-solution unit is a closed system and is not dependent upon entry of external air during administration.

12 CLINICAL PHARMACOLOGY

12.1 Mechanism of Action

ADDITIVE SOLUTION FORMULA 3 acts to preserve and extend the shelf life of packed RBC products for later transfusion to patients. The following ingredients are key components of the solution:

- Adenine to support adenosine triphosphate (ATP) levels
- Citrate for membrane protection, anticoagulation and pH regulation
- Sodium (Sodium Chloride and Sodium Citrate) and dextrose for isotonicity
- Dextrose for RBC nutrition

This solution has no pharmacological effect.

14 CLINICAL STUDIES

The in vivo and in vitro quality of RBCs stored for 42 days in ADDITIVE SOLUTION FORMULA 3 (AS-3) storage solution has been assessed in three clinical studies.

In Vivo Recovery of Autologous Radiolabeled RBC

A single-arm, multicenter, in vivo study was conducted to assess the recovery of radiolabeled RBCs 24 hours post infusion. Acceptability of in vivo recovery was determined using established FDA-CBER acceptance criteria. Double collection RBCs (dRBC) were collected using the Trima Accel system and stored in ADDITIVE SOLUTION FORMULA 3 (AS-3) solution for 42 days, then radiolabeled with ^51Chromium, and transfused back to the original subject. Table 2 summarizes the in vivo recovery data. Of the 27 units transfused, 26 had > 75% RBC recovery.

Table 2: In vivo Radiolabeled RBC Recovery
Outcome Measure | Study Site (N) | Average (SD) | Min, Max
Overall Day 42 infused, 24-hour RBC Radiolabel Recovery (%) | Site 1 (12) | 79.3 (5.6) | 67.5, 86.5
Overall Day 42 infused, 24-hour RBC Radiolabel Recovery (%) | Site 2 (15) | 87.1 (5.5) | 79.0, 98.1
Abbreviations: Max= Maximum, Min= Minimum, N= Number of Units Transfused, RBC= Red Blood Cell, SD= Standard Deviation

FDA-CBER Criteria for Acceptable Recovery: Radiolabeled RBC recoveries should average at least 75%, with a standard deviation of at most 9%. In addition, the 95% one-sided lower confidence limit for the population proportion of successes should be > 70%, with success being defined as an individual red blood cell in vivo recovery of at least 75%. No more than 3 out of 24 data points may have less than 75% radiolabeled red cell recovery at 24 hours post infusion.

The primary outcome was met for RBCs collected on the Trima Accel system and stored in ADDITIVE SOLUTION FORMULA 3 (AS-3) storage solution.

In Vitro RBC Quality Studies

The in vitro quality of RBCs collected in single RBC collection (sRBC) and dRBC procedures using the Trima Accel system was assessed after 42 days of storage in ADDITIVE SOLUTION FORMULA 3 (AS-3) solution in a multicenter, paired study. In vitro quality was determined using established FDA-CBER acceptance criteria. The quality of RBCs stored in ADDITIVE SOLUTION FORMULA 3 (AS-3) solution (test) was compared to RBCs stored in plasma (control). Table summarizes the in vitro RBC quality data for collection on the Trima Accel system and storage in ADDITIVE SOLUTION FORMULA 3 (AS-3) solution.

Table 3: In Vitro Quality Measures for RBCs Collected using the Trima Accel System and Stored in ADDITIVE SOLUTION FORMULA 3 (AS-3)
Outcome Measure | Site (N) | Average (SD) | Min, Max
Day 42 Hemolysis for Single RBC Collection [Percent hemolysis was calculated from plasma free hemoglobin using the equation: %Hemolysis = (100 – RBC Product HCT)* Plasma Hgb / (RBC Product Hgb).] (%) | Site 1 (32) | 0.16 (0.06) | 0.06, 0.33
Day 42 Hemolysis for Single RBC Collection [Percent hemolysis was calculated from plasma free hemoglobin using the equation: %Hemolysis = (100 – RBC Product HCT)* Plasma Hgb / (RBC Product Hgb).] (%) | Site 2 (18) | 0.34 (0.18) | 0.12, 0.70
Day 42 Hemolysis for Single RBC Collection [Percent hemolysis was calculated from plasma free hemoglobin using the equation: %Hemolysis = (100 – RBC Product HCT)* Plasma Hgb / (RBC Product Hgb).] (%) | Site 3 (18) | 0.26 (0.11) | 0.09, 0.47
Day 42 Hemolysis for Double RBC Collection (%) | Site 1 (25) | 0.15 (0.05) | 0.06, 0.29
Day 42 Hemolysis for Double RBC Collection (%) | Site 2 (24) | 0.39 (0.19) | 0.16, 0.95
Day 42 Hemolysis for Double RBC Collection (%) | Site 3 (21) | 0.26 (0.12) | 0.13, 0.61
Change in pH from Day 0 to Day 42 for Single RBC Collection [The difference in pH between Test and Control on Day 42 was calculated as: ΔpH = │pHTest – pHControl│ ≤ 0.5 where the difference was expected to be less than or equal to 0.5 pH units.] | Site 1 (31) | 0.03 (0.02) | 0.00, 0.08
Change in pH from Day 0 to Day 42 for Single RBC Collection [The difference in pH between Test and Control on Day 42 was calculated as: ΔpH = │pHTest – pHControl│ ≤ 0.5 where the difference was expected to be less than or equal to 0.5 pH units.] | Site 2 (18) | 0.03 (0.03) | 0.00, 0.11
Change in pH from Day 0 to Day 42 for Single RBC Collection [The difference in pH between Test and Control on Day 42 was calculated as: ΔpH = │pHTest – pHControl│ ≤ 0.5 where the difference was expected to be less than or equal to 0.5 pH units.] | Site 3 (16) | 0.02 (0.02) | 0.00, 0.07
Change in pH from Day 0 to Day 42 for Double RBC Collection | Site 1 (23) | 0.02 (0.02) | 0.00, 0.05
Change in pH from Day 0 to Day 42 for Double RBC Collection | Site 2 (23) | 0.02 (0.03) | 0.00, 0.15
Change in pH from Day 0 to Day 42 for Double RBC Collection | Site 3 (19) | 0.02 (0.02) | 0.00, 0.08
Ratio of ATP Retention for Single Collection RBC Units (test/control) [ATP retention was determined for test and control units across all sites and calculated as ATP Level on Day 42 / ATP Level on Day 0.] | All sites (65) | 1.02 (0.18) | 0.46, 1.47
Ratio of ATP Retention for Double Collection RBC Units (test/control) | All sites (65) | 1.07 (0.19) | 0.55, 1.51
Ratio of the Normalized Leaked Potassium for Single Collection RBC Units (test/control) [Normalized potassium was calculated by determining the total number of millimoles of potassium leaked from the RBCs into the supernatant volume and dividing this by the total hemoglobin in the stored product. Normalized Leaked Potassium = Volume*(1-Hct/100)*(d42[K+] – d0[K+]) / Total Hemoglobin] | All sites (65) | 0.98 (0.07) | 0.76, 1.13
Ratio of the Normalized Leaked Potassium for Double Collection RBC Units (test/control) | All Sites (64) | 1.00 (0.08) | 0.85, 1.24
Abbreviations: HCT = hematocrit, HgB = hemoglobin, Max = Maximum, Min = Minimum, N = Number of Units, RBC = Red Blood Cell, SD = Standard Deviation

FDA-CBER Criteria for Acceptable Day 42 Hemolysis: Zero failures (hemolysis ≥ 1% after 42-day storage) out of 60 test units that were not excluded from analysis by the Extreme Studentized Deviate test with α=0.05, which satisfies the binomial distribution testing requirement that, with 95% probability and a one-sided 95% lower confidence limit, the post-storage hemolysis was less than 1% per unit.

There were 0/68 sRBC test units and 0/70 dRBC test units with Day 42 hemolysis ≥ 1%. No donors were excluded as hemolysis was < 1% for all test units. Therefore, the primary objective was met for RBCs stored in ADDITIVE SOLUTION FORMULA 3 (AS-3).

The in vitro quality of sRBC and dRBC units collected using the Trima Accel system was assessed after 42 days of storage in AS-3 solution in a multicenter study. The quality of RBCs was compared between sRBC and dRBC units, and between units A and B of the dRBC collection. Table summarizes the in vitro RBC quality data for collection using the Trima Accel system and storage in ADDITIVE SOLUTION FORMULA 3 (AS-3).

Table 4: In Vitro Quality Measures for RBCs Collected using the Trima Accel System and Stored in ADDITIVE SOLUTION FORMULA 3 (AS-3)
Outcome Measure [All outcome measures are shown after 42 days of storage in AS-3 solution.] | Site | RBC Unit |  |  | P Value [All comparisons were performed using a Student's T-test. A 2-tailed paired comparison was performed for dRBC A v dRBC B. A 2-tailed, two sample, equal variance comparison was performed for sRBC v dRBC units.]
Outcome Measure [All outcome measures are shown after 42 days of storage in AS-3 solution.] | Site | dRBC A | dRBC B | sRBC | dRBC A v dRBC B | sRBC v dRBC
Hematocrit (%), mean (SD) | Site 1 | 54.4 (3.7) | 53.9 (3.6) | 55.8 (4.4) | 0.132 | 0.253
Hematocrit (%), mean (SD) | Site 2 | 56.0 (3.9) | 53.3 (11.6) | 58.4 (3.6) | 0.398 | 0.149
pH, mean (SD) | Site 1 | 6.4 (0.04) | 6.4 (0.05) | 6.5 (0.08) | 0.760 | 0.643
pH, mean (SD) | Site 2 | 6.4 (0.1) | 6.4 (0.1) | 6.4 (0.1) | 0.175 | 0.217
pCO2, mean (SD) | Site 1 | 140 (8) | 137 (8) | 139 (12) | 0.172 | 0.525
pCO2, mean (SD) | Site 2 | 130.5 (11.7) | 130.4 (12.4) | 125.6 (11.1) | 1.00 | 0.316
pO2, mean (SD) | Site 1 | 46 (7) | 47 (7) | 46 (7) | 0.104 | 0.825
pO2, mean (SD) | Site 2 | 52.0 (10.6) | 51.4 (12.5) | 46.2 (3.4) | 0.878 | 0.157
ATP (μmols/g HB), mean (SD) | Site 1 | 2.6 (0.6) | 2.6 (0.6) | 2.9 (0.5) | 0.759 | 0.306
ATP (μmols/g HB), mean (SD) | Site 2 | 3.0 (0.5) | 3.0 (0.6) | 2.6 (0.5) | 0.845 | 0.110
K (mEq/L), mean (SD) | Site 1 | 46.5 (7.9) | 47.5 (8.2) | 49.3 (10.1) | 0.396 | 0.620
K (mEq/L), mean (SD) | Site 2 | 40.5 (5.8) | 41.1 (5.9) | 44.7 (5.7) | 0.575 | 0.128
Na (mEq/L), mean (SD) | Site 1 | 122 (7) | 123 (6) | 126 (17) | 0.016 | 0.609
Na (mEq/L), mean (SD) | Site 2 | 105.6 (5.4) | 104.2 (5.5) | 100.0 (5.5) | 0.004 | 0.069
Total Hemoglobin (g/dL) | Site 1 | 60.5 (5.8) | 60.0 (5.3) | 61.0 (4.7) | 0.546 | 0.627
Total Hemoglobin (g/dL) | Site 2 | 58.5 (5.5) | 59.6 (5.8) | 60.3 (5.0) | 0.264 | 0.747
Plasma Hemoglobin (mg/dL), mean (SD) | Site 1 | 149.9 (151.6) | 141.2 (145.3) | 152.7 (86.3) | 0.034 | 0.815
Plasma Hemoglobin (mg/dL), mean (SD) | Site 2 | 139.0 (61.0) | 126.7 (80.4) | 135.5 (82.1) | 0.241 | 0.790
Hemolysis (%), mean (SD) | Site 1 | 0.33 (0.34) | 0.32 (0.34) | 0.30 (0.15) | 0.05 | 0.855
Hemolysis (%), mean (SD) | Site 2 | 0.34 (0.13) | 0.31 (0.16) | 0.31 (0.19) | 0.363 | 0.995
Osmotic Fragility [Osmotic fragility was measured as percent hemolysis in 0.55% saline at Site 1 and as the percent saline at ≥ 50% hemolysis at Site 2.] | Site 1 | 20.0 (14.4) | 19.6 (15.2) | 31.0 (22.3) | 0.885 | 0.152
Osmotic Fragility [Osmotic fragility was measured as percent hemolysis in 0.55% saline at Site 1 and as the percent saline at ≥ 50% hemolysis at Site 2.] | Site 2 | 0.51 (0.03) | 0.51 (0.03) | 0.49 (0.02) | 0.935 | 0.009
Abbreviations: dRBC A = Unit A of the Double Red Blood Cell Collection, dRBC B = Unit B of the Double Red Blood Cell Collection, sRBC = Single Red Blood Cell Unit, SD = Standard Deviation

The primary outcome of this study was to demonstrate RBC collection, storage, and viability in vitro.

The sRBC and dRBC units collected were comparable. The hematocrits, blood gasses, ATP, potassium, total hemoglobin, and osmotic fragility were within acceptable ranges following storage. Two statistically significant differences were identified between the A and B units in the dRBC collection at Day 42 (sodium and plasma free hemoglobin), but these differences were not clinically significant. There was no difference between dRBC units in hemolysis following storage in ADDITIVE SOLUTION FORMULA 3 (AS-3). A statistically significant difference was identified in the osmotic fragility of RBCs stored in ADDITIVE SOLUTION FORMULA 3 (AS-3) following sRBC collection or dRBC collection at Day 42, but the difference was not clinically significant. All the RBC units collected averaged less than 1% hemolysis on Day 42. These results are consistent with US and European guidelines for hemolysis on transfusion. ATP recovery was greater than 70% of all units, which is predictive of good in vivo viability, and potassium levels on Day 42 average less than 50 mEq/L indicating good RBC membrane stability over the storage period.

16 HOW SUPPLIED/STORAGE AND HANDLING

ADDITIVE SOLUTION FORMULA 3 (AS-3) is a clear solution supplied in sterile and non-pyrogenic Polyolefin bags.

SIZE | CATALOG NUMBER | NDC NUMBER | QUANTITY PER CASE
100 mL | 40832 | 14537-832-03 | 36
200 mL | 40833 | 14537-833-03 | 30
350 mL | 40834 | 14537-834-03 | 24

STORAGE

Up to 25 °C.

Protect from freezing.

Issued: TBD

Manufactured by
Terumo BCT, Inc.
Lakewood, CO 80215

PRINCIPAL DISPLAY PANEL - 100 mL Bag Pouch Case Label

Additive Solution Formula 3 (AS-3)

Catalog # 40832 Polyolefin Bag 6 x 6 x 100 mL units
NDC 14537-832-03

Manufactured by TERUMO BCT, INC.
10811 W. Collins Ave.,
Lakewood CO 80215, USA
Made in UK
LPN 1000005747

Use only with Trima Accel red blood cell apheresis collections. See
apheresis device operator's manual for complete instructions. Read the
package insert before use. Sterile. Non-pyrogenic. Sterilized with steam.
Caution: Do not use if the bag is damaged. Use only if solution is clear
and free of particulate matter. Single use bag. Discard any unused
product. Not for direct intravenous infusion. Rx Only.
Recommended storage: Up to 25°C. Protect from freezing.
Each 100 mL contains:
Dextrose Monohydrate USP
1.10 g
Trisodium Citrate Dihydrate USP
0.588 g
Sodium Chloride USP
0.410 g
Monobasic Sodium Phosphate Monohydrate USP
0.276 g
Citric Acid Monohydrate USP
0.042 g
Adenine USP
0.030 g
In Water for Injection USP

Lot
Expiry Date

PRINCIPAL DISPLAY PANEL - 200 mL Bag Case Label

Additive Solution Formula 3 (AS-3)

Catalog # 40833 Polyolefin Bag 30 x 200 mL units
NDC 14537-833-03

Manufactured by TERUMO BCT, INC.
10811 W. Collins Ave.,
Lakewood CO 80215, USA
Made in UK
LPN 1000005752

Use only with Trima Accel red blood cell apheresis collections. See
apheresis device operator's manual for complete instructions. Read the
package insert before use. Sterile. Non-pyrogenic. Sterilized with steam.
Caution: Do not use if the bag is damaged. Use only if solution is clear
and free of particulate matter. Single use bag. Discard any unused
product. Not for direct intravenous infusion. Rx Only.
Recommended storage: Up to 25°C. Protect from freezing.
Each 100 mL contains:
Dextrose Monohydrate USP
1.10 g
Trisodium Citrate Dihydrate USP
0.588 g
Sodium Chloride USP
0.410 g
Monobasic Sodium Phosphate Monohydrate USP
0.276 g
Citric Acid Monohydrate USP
0.042 g
Adenine USP
0.030 g
In Water for Injection USP

Lot
Expiry Date

PRINCIPAL DISPLAY PANEL - 350 mL Bag Case Label

Additive Solution Formula 3 (AS-3)

Catalog # 40834 Polyolefin Bag 24 x 350 mL units
NDC 14537-834-03

Manufactured by TERUMO BCT, INC.
10811 W. Collins Ave.,
Lakewood CO 80215, USA
Made in UK
LPN 1000005753

Use only with Trima Accel red blood cell apheresis collections. See
apheresis device operator's manual for complete instructions. Read the
package insert before use. Sterile. Non-pyrogenic. Sterilized with steam.
Caution: Do not use if the bag is damaged. Use only if solution is clear
and free of particulate matter. Single use bag. Discard any unused
product. Not for direct intravenous infusion. Rx Only.
Recommended storage: Up to 25°C. Protect from freezing.
Each 100 mL contains:
Dextrose Monohydrate USP
1.10 g
Trisodium Citrate Dihydrate USP
0.588 g
Sodium Chloride USP
0.410 g
Monobasic Sodium Phosphate Monohydrate USP
0.276 g
Citric Acid Monohydrate USP
0.042 g
Adenine USP
0.030 g
In Water for Injection USP

Lot
Expiry Date